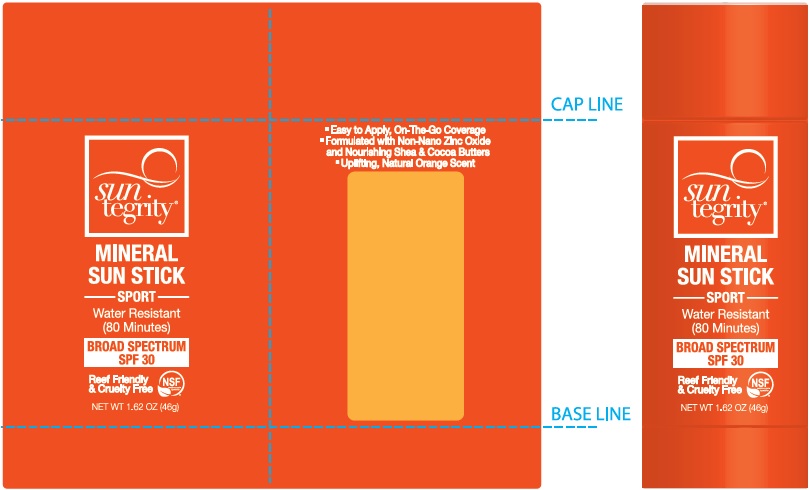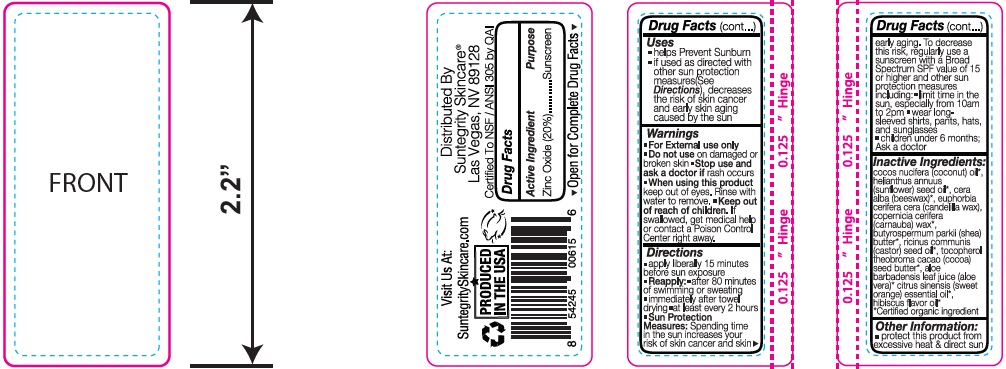 DRUG LABEL: SUNSCREEN
NDC: 62932-174 | Form: OINTMENT
Manufacturer: Private Label Select Ltd CO
Category: otc | Type: HUMAN OTC DRUG LABEL
Date: 20200715

ACTIVE INGREDIENTS: ZINC OXIDE 50 g/100 g
INACTIVE INGREDIENTS: GERANIOL; .BETA.-CITRONELLOL, (+/-)-; COCOA BUTTER; ALOE VERA LEAF; CANDELILLA WAX; SHEA BUTTER; CITRUS SINENSIS FLOWER OIL; TOCOPHEROL; LINALOOL, (+/-)-; SUNFLOWER OIL; CARNAUBA WAX; CASTOR OIL; WHITE WAX; COCONUT OIL

50g Suntegrity Sunstick SPF30